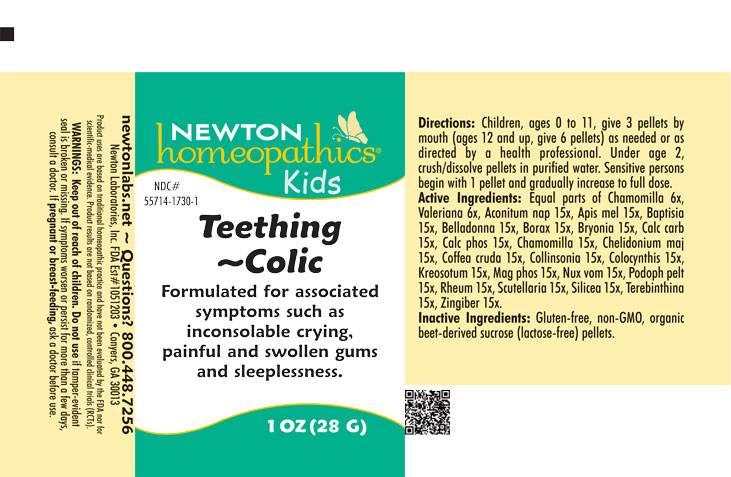 DRUG LABEL: Teething-Colic
NDC: 55714-1730 | Form: PELLET
Manufacturer: Newton Laboratories, Inc.
Category: homeopathic | Type: HUMAN OTC DRUG LABEL
Date: 20251106

ACTIVE INGREDIENTS: VALERIAN 6 [hp_X]/1 g; COLLINSONIA CANADENSIS ROOT 15 [hp_X]/1 g; APIS MELLIFERA 15 [hp_X]/1 g; BAPTISIA TINCTORIA ROOT 15 [hp_X]/1 g; ATROPA BELLADONNA 15 [hp_X]/1 g; SODIUM BORATE 15 [hp_X]/1 g; BRYONIA ALBA ROOT 15 [hp_X]/1 g; OYSTER SHELL CALCIUM CARBONATE, CRUDE 15 [hp_X]/1 g; TRIBASIC CALCIUM PHOSPHATE 15 [hp_X]/1 g; MATRICARIA CHAMOMILLA 15 [hp_X]/1 g; CHELIDONIUM MAJUS 15 [hp_X]/1 g; ARABICA COFFEE BEAN 15 [hp_X]/1 g; WOOD CREOSOTE 15 [hp_X]/1 g; MAGNESIUM PHOSPHATE, DIBASIC TRIHYDRATE 15 [hp_X]/1 g; STRYCHNOS NUX-VOMICA SEED 15 [hp_X]/1 g; PODOPHYLLUM 15 [hp_X]/1 g; RHEUM OFFICINALE ROOT 15 [hp_X]/1 g; SCUTELLARIA LATERIFLORA WHOLE 15 [hp_X]/1 g; SILICON DIOXIDE 15 [hp_X]/1 g; TURPENTINE OIL 15 [hp_X]/1 g; GINGER 15 [hp_X]/1 g; CITRULLUS COLOCYNTHIS FRUIT PULP 15 [hp_X]/1 g; ACONITUM NAPELLUS 15 [hp_X]/1 g
INACTIVE INGREDIENTS: SUCROSE

Teething 1730P

INDICATIONS AND USAGE SECTION

Formuated for associated symptoms such as inconsolable crying, painful and swollen gums and sleeplessness.

DOSAGE & ADMINISTRATION SECTION

Directions: Children, ages 0 to 11, give 3 pellets by mouth (ages 12 and up, give 6 pellets) as needed or a directed by a health professional. Under age 2, crush/dissolve pellets in purified water. Sensitive person begin with 1 pellet and gradually increase to full dose.

OTC - ACTIVE INGREDIENT SECTION

Equal parts of Chamomilla 6x, Valeriana officinalis 6x, Aconitum napellus 15x, Apis mellifica 15x, Baptisia tinctoria 15x, Belladonna 15x, Borax 15x, Bryonia 15x, Calcarea carbonica 15x, Calcarea phosphorica 15x, Chamomilla 15x, Chelidonium majus 15x, Coffea cruda 15x, Collinsonia canadensis 15x, Colocynthis 15x, Kreosotum 15x, Magnesia phosphorica 15x, Nux vomica 15x, Podophyllum peltatum 15x, Rheum 15x, Scutellaria lateriflora 15x, Silicea 15x, Terebinthina 15x, Zingiber officinale 15x.

OTC - PURPOSE SECTION

Formuated for associated symptoms such as inconsolable crying, painful and swollen gums and sleeplessness.

INACTIVE INGREDIENT SECTION

Gluten-free, non-GMO, organic beet-derived sucrose (lactose-free) pellets.

QUESTIONS SECTION

newtonlabs.net – Questions? 800.448.7256

Newton Laboratories, Inc. FDA Est # 1051203 - Conyers, GA 30013

WARNINGS SECTION

WARNINGS: Keep out of reach of children. Do not use if tamper-evident seal is broken or missing. If symptoms worsen or persist for more than a few days, consult a doctor. If pregnant or breast-feeding, ask a doctor before use.

OTC - PREGNANCY OR BREAST FEEDING SECTION

If pregnant or breast-feeding, ask a doctor before use.

OTC - KEEP OUT OF REACH OF CHILDREN SECTION

WARNINGS: Keep out of reach of children.